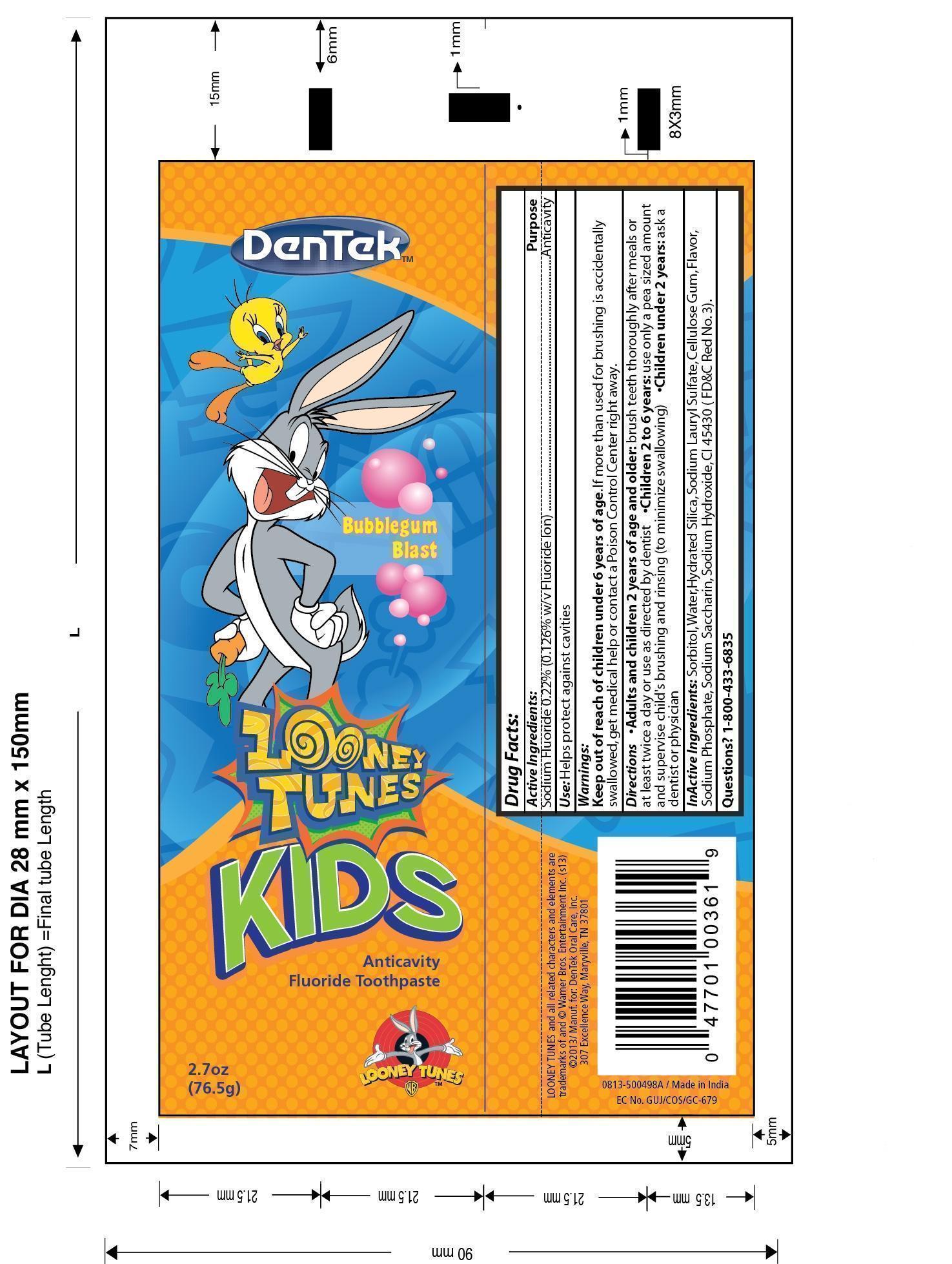 DRUG LABEL: DenTek Kids Anticavity Fluoride
NDC: 60630-498 | Form: PASTE, DENTIFRICE
Manufacturer: DenTek Oral Care, Inc.
Category: otc | Type: HUMAN OTC DRUG LABEL
Date: 20131001

ACTIVE INGREDIENTS: SODIUM FLUORIDE 0.0964 g/76.5 g
INACTIVE INGREDIENTS: SORBITOL 42.075 g/76.5 g; WATER 15.34 g/76.5 g; HYDRATED SILICA 15.3 g/76.5 g; SODIUM LAURYL SULFATE 1.3 g/76.5 g; CARBOXYMETHYLCELLULOSE SODIUM 0.918 g/76.5 g; SODIUM PHOSPHATE 0.38 g/76.5 g; SACCHARIN SODIUM DIHYDRATE 0.176 g/76.5 g; SODIUM HYDROXIDE 0.0765 g/76.5 g

Kids Toothpaste with sodium fluoride

Active Ingredients

Sodium Fluoride 0.22% (0.126% w/v Fluoride Ion)

Purpose

Anticavity

Indications and Use

Use: Helps protect against cavities

Warnings

Keep out of reach of children under 6 years of age. If more than used for brushing is accidentally swallowed, get medical help or contact a Poison Control Center right away.

Directions

.Adults and children 2 years of age and older: brush teeth thoroughly after meals or at least twice a day or use as directed by dentist .Children 2 to 6 years: use only a pea sized amount and supervise child's brushing and rinsing (to minimize swallowing) .Children under 2 years: ask a dentist or physician

Inactive Ingredients

Sorbitol, Water, Hydrated Silica, Sodium Lauryl Sulfate, Cellulose Gum, Flavor, Sodium Phosphate, Sodium Saccharin, Sodium Hydroxide, CI 45430 (FD&C Red No. 3).

Questions

Questions? 1-800-433-6835

Keep out of reach of children under 6 years of age.